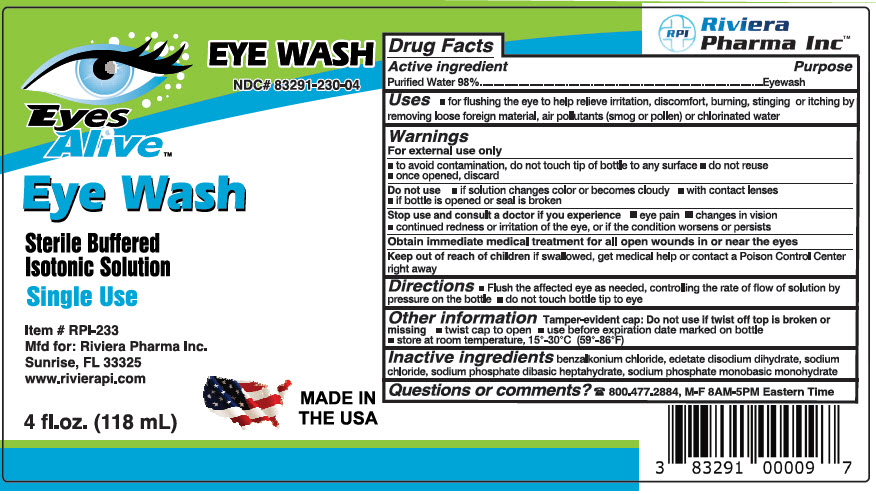 DRUG LABEL: Eyes Alive Eye Wash
NDC: 83291-230 | Form: SOLUTION
Manufacturer: RIVIERA PHARMA INC
Category: otc | Type: HUMAN OTC DRUG LABEL
Date: 20240605

ACTIVE INGREDIENTS: Water 980 mg/1 mL
INACTIVE INGREDIENTS: Benzalkonium chloride; edetate disodium; sodium chloride; sodium phosphate, dibasic, heptahydrate; sodium phosphate, monobasic, monohydrate

Eyes Alive™ Eye Wash

Drug Facts

Active Ingredient

Purified Water 98%

Purpose

Eyewash

Uses

For flushing the eye to help relieve irritation, discomfort, burning, stinging or itching by removing loose foreign material, air pollutants (smog or pollen) or chlorinated water.

Warnings

For external use only

- To avoid contamination, do not touch tip of bottle to any surface
- Do not reuse
- Once opened, discard

Do not use

If solution changes colors or becomes cloudy

- With contact lenses
- If bottle is opened or seal is broken

Stop use and consult a doctor if you experience

Eye pain

- Changes in vision
- Continued redness or irritation of the eye or if the condition worsen or persists.

Obtain immediate medical treatment for all open wounds in or near the eyes.

Keep out of reach of children

If swallowed, get medical help or contact a Poison Control Center right away.

Directions

Flush the affected eye as needed, controlling the rate of flow of solution by pressure on the bottle

Do not touch bottle tip to eye

Other Information

Tamper-evident cap: Do not use if twist off top is broken or missing

- Twist cap to open
- Use before expiration date marked on bottle
- Store at room temperature, 15°-30° C (59° to 86°F).

Inactive Ingredients

Benzalkonium chloride, edetate disodium dihydrate, sodium chloride, sodium phosphate dibasic heptahydrate, sodium phosphate monobasic monohydrate.

Questions or Comments?

Call 800.477.2884, M-F 9 am-5 pm Eastern time

PRINCIPAL DISPLAY PANEL - 118 mL Bottle Label

EYE WASH
NDC# 83291-230-04

Eyes
Alive™

Eye Wash

Sterile Buffered
Isotonic Solution

Single Use

Item # RPI-233
Mfd. For: Riviera Pharma, Inc.
Sunrise, FL 33325
www.rivierapi.com

4 fl.oz. (118 mL)

MADE IN
THE USA